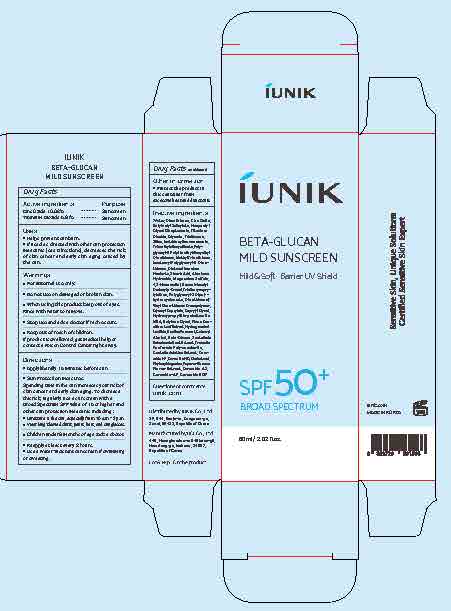 DRUG LABEL: BETA-GLUCAN MILD SUNSCREEN
NDC: 83403-101 | Form: LOTION
Manufacturer: IUNIK Co., Ltd
Category: otc | Type: HUMAN OTC DRUG LABEL
Date: 20260107

ACTIVE INGREDIENTS: ZINC OXIDE 10.08 g/100 mL; TITANIUM DIOXIDE 5.61 g/100 mL
INACTIVE INGREDIENTS: DISTEARDIMONIUM HECTORITE; GLYCERYL CAPRYLATE; BACILLUS POLYFERMENTICUS; CHOLESTEROL; WATER; PINUS DENSIFLORA LEAF; POLYGLYCERYL-2 DIPOLYHYDROXYSTEARATE; CAPRYLYL GLYCOL; POLYGLYCERYL-3 POLYDIMETHYLSILOXYETHYL DIMETHICONE (4000 MPA.S); DIMETHICONE/POLYGLYCERIN-3 CROSSPOLYMER; CERAMIDE NG; PAPAVER RHOEAS FLOWER; BUTYLOCTYL SALICYLATE; TRISILOXANE; DIMETHICONE; SILICA; CENTELLA ASIATICA TRITERPENOIDS; NEOPENTYL GLYCOL DIHEPTANOATE; TRIETHOXYCAPRYLYLSILANE; CETEARYL ALCOHOL; ODETIGLUCAN; CERAMIDE AP; ALUMINUM HYDROXIDE; ISOTRIDECYL ISONONANOATE; METHYL TRIMETHICONE; STEARIC ACID; MAGNESIUM SULFATE; 1,2-HEXANEDIOL; BENZOTRIAZOLYL DODECYL P-CRESOL; DIMETHICONE/VINYL DIMETHICONE CROSSPOLYMER (SOFT PARTICLE); HYDROXYPROPYL BISPALMITAMIDE MEA; BUTYLENE GLYCOL; SCUTELLARIA BAICALENSIS ROOT; TREMELLA FUCIFORMIS WHOLE; TRIMETHYLSILOXYSILICATE (M/Q 0.6-0.8); CERAMIDE 4; GLYCERIN; HYDROGENATED SOYBEAN LECITHIN; CERAMIDE NP; PHYTOSPHINGOSINE; CERAMIDE 1

BETA-GLUCAN MILD SUNSCREEN

ACTIVE INGREDIENTS

Titamiun Dioxide 5.61%

Zinc Oxide 10.08%

PURPOSE

Sunscreen

USES

- Helps prevent sunburn.

- If used as directed with other sun protection measures (see Directions), decreases the risk of skin cancer and early skin aging caused by the sun.

WARNINGS

- For external use only.
- Do not use on damaged or broken skin.
- When using this product keep out of eyes. Rinse with water to remove.
- Stop use and ask a doctor if rash occurs.
- Keep out of reach of children. If product is swallowed, get medical help or contact a Poison Control Center right away.

KEEP OUT OF REACH OF CHILDREN

- If product is swallowed, get medical help or contact a Poison Control Center right away.

DIRECTIONS

- Apply liberally 15 minutes before sun exposure.
- Sun protection measures.

- Spending time in the sun increases your risk of skin cancer and early skin aging. To decrease this risk, regularly use a sunscreen with a Broad Spectrum SPF value of 15 or higher and other sun protection measures including:

- Limit time in the sun, especially from 10 a.m.–2 p.m.
- Wear long-sleeved shirts, pants, hats, and sunglasses.
- Children under 6 months of age: Ask a doctor.
- Reapply at least every 2 hours.
- Use a water resistant sunscreen if swimming or sweating.

INACTIVE INGREDIENTS

Water, Dimethicone, Butyloctyl Salicylate, Neopentyl Glycol Diheptanoate, Glycerin, Trisiloxane, Silica, Isotridecyl Isononanoate, Trimethylsiloxysilicate, Polyglyceryl-3 Polydimethylsiloxyethyl Dimethicone, Methyl Trimethicone, Isostearyl Polyglyceryl-3 Dimethicone, Disteardimonium Hectorite, Stearic Acid, Aluminum Hydroxide, Magnesium Sulfate, 1,2-Hexanediol, Benzotriazolyl Dodecyl p-Cresol, Triethoxycaprylylsilane, Polyglyceryl-2 Dipolyhydroxystearate, Dimethicone/Vinyl Dimethicone Crosspolymer, Glyceryl Caprylate, Caprylyl Glycol, Hydroxypropyl Bispalmitamide MEA, Butylene Glycol, Pinus Densiflora Leaf Extract, Hydrogenated Lecithin, Bacillus Ferment, Cetearyl Alcohol, Beta-Glucan, Scutellaria Baicalensis Root Extract, Tremella Fuciformis Polysaccharide, Centella Asiatica Extract, Ceramide NP, Ceramide NG, Cholesterol, Phytosphingosine, Papaver Rhoeas Flower Extract, Ceramide AS, Ceramide AP, Ceramide EOP

BETA-GLUCAN MILD SUNSCREEN